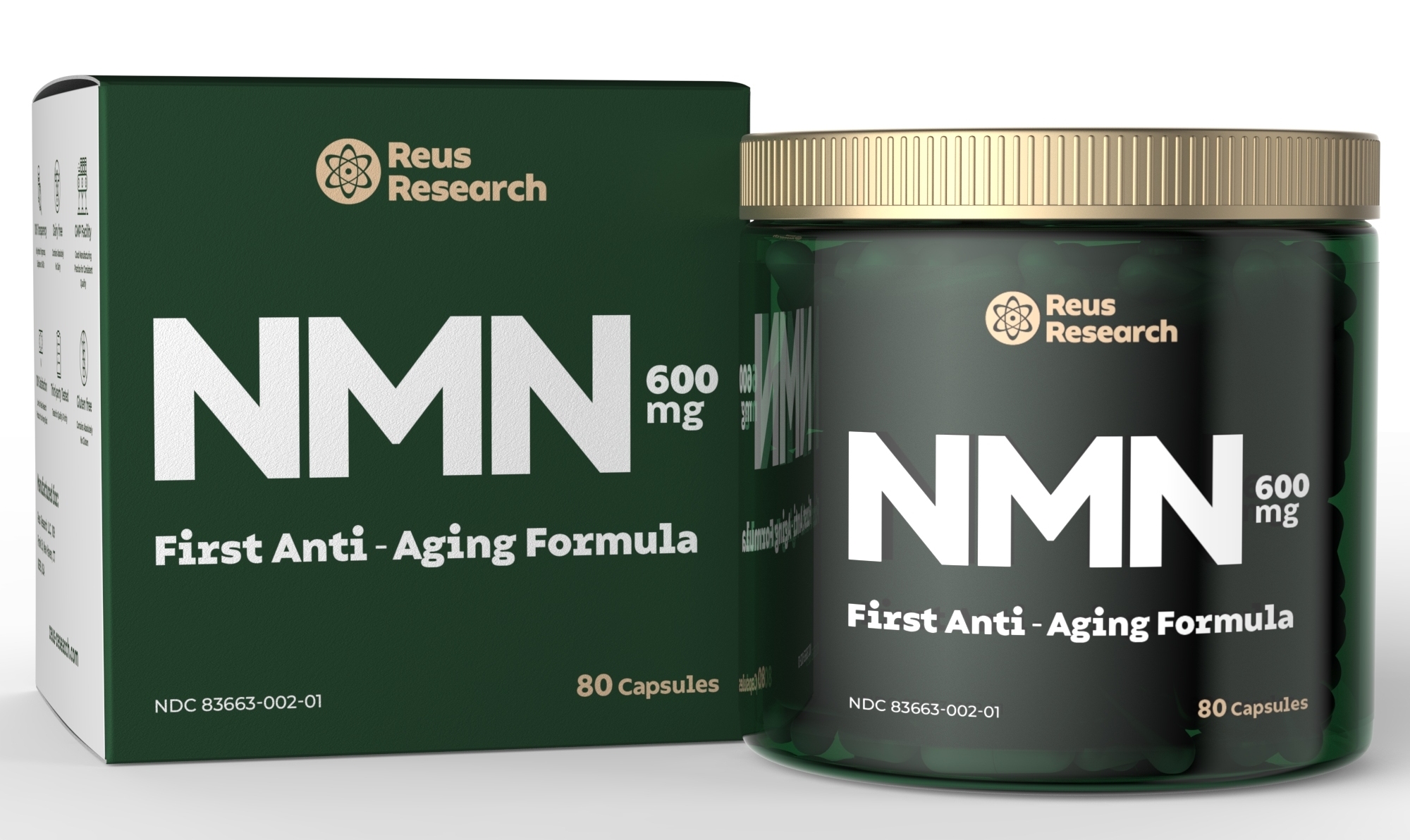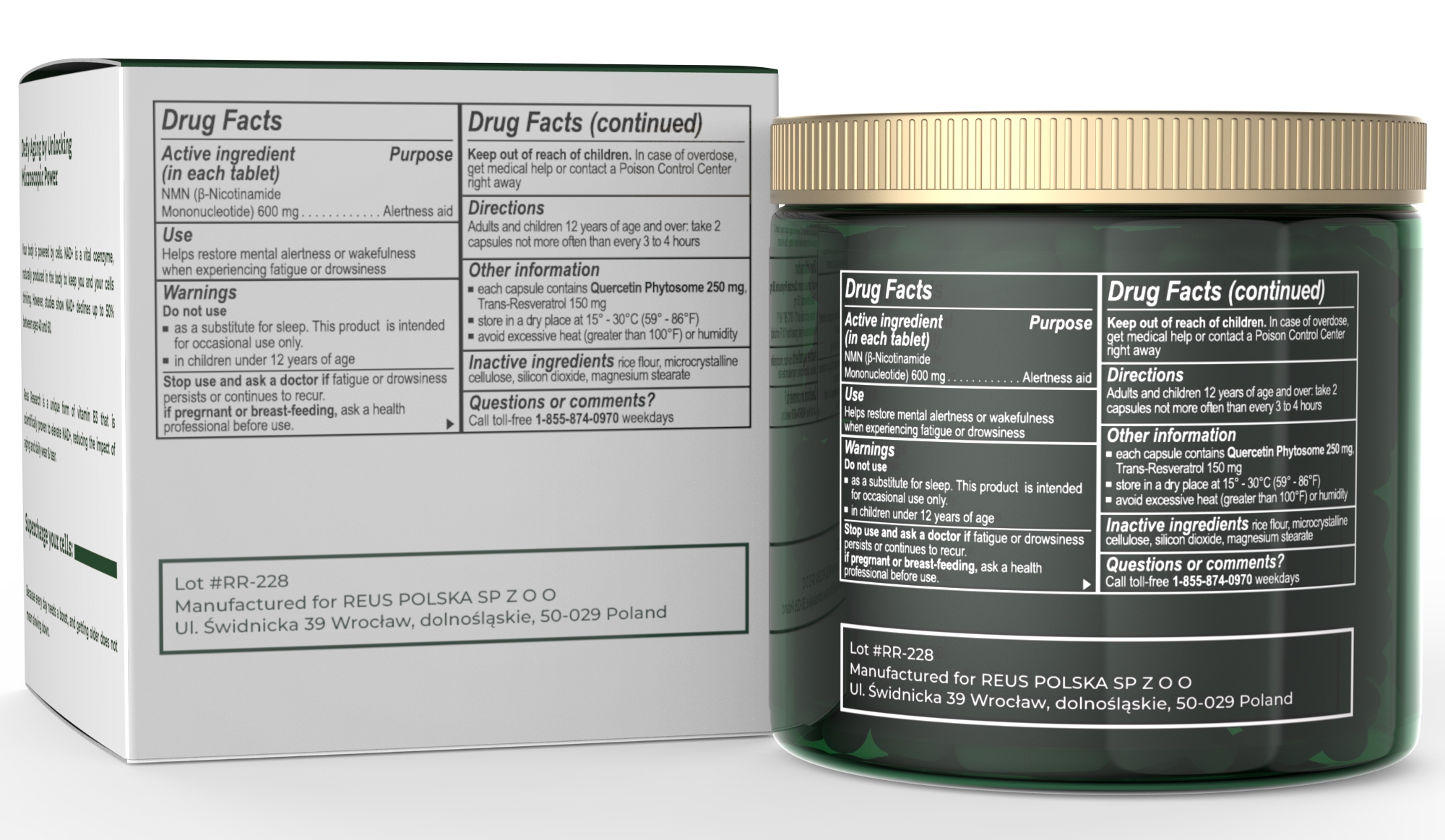 DRUG LABEL: REUS NR
NDC: 83663-002 | Form: CAPSULE
Manufacturer: REUS POLSKA SP Z O O
Category: otc | Type: HUMAN OTC DRUG LABEL
Date: 20230829

ACTIVE INGREDIENTS: NICOTINAMIDE MONONUCLEOTIDE 600 mg/1 1
INACTIVE INGREDIENTS: RESVERATROL 150 mg/1 1

INACTIVE INGREDIENT

Silicon dioxide

Instructions on box

Do not Use

as a substitute for sleep. This product is intended for accosional use only

in children under 12 years of age

Warnings:

Do not use:

1. as a substitute for sleep. This product is intended for occasional use only.

2. in children under 12 years of age.

3. If pregnant or breastfeeding, consult a healthcare professional before use.

4. Keep out of reach of children. In case of overdose, seek immediate medical attention or contact a poison control center.

5. Stop use and ask a doctor if fatigue or drowsiness persists or continues to recur.

ACTIVE INGREDIENT

β-Nicotinamide Mononucleotide 600mg

Keep out of reach of children.

In case of overdose, get medical help or contact a Poison control center right away.

PREGNANCY OR BREAST FEEDING

If pregnant or breast feeding, ask a health professional before use.

INDICATIONS AND USAGE

Helps restore mental alertness or wafulness when experiencing fatigue or drowsiness

Adults and Children 12 years of age and over: take 2 capsules not more often than every 3 to 4 hours.

PURPOSE

Alertness aid

DOSAGE AND ADMINISTRATION

each capsule contains Quercetin Phytosome 250mg, Trans-Resveratrol 150 mg

STORAGE AND HANDLING

Store in a dry place at 15oC - 30oC (59oF - 86oF)